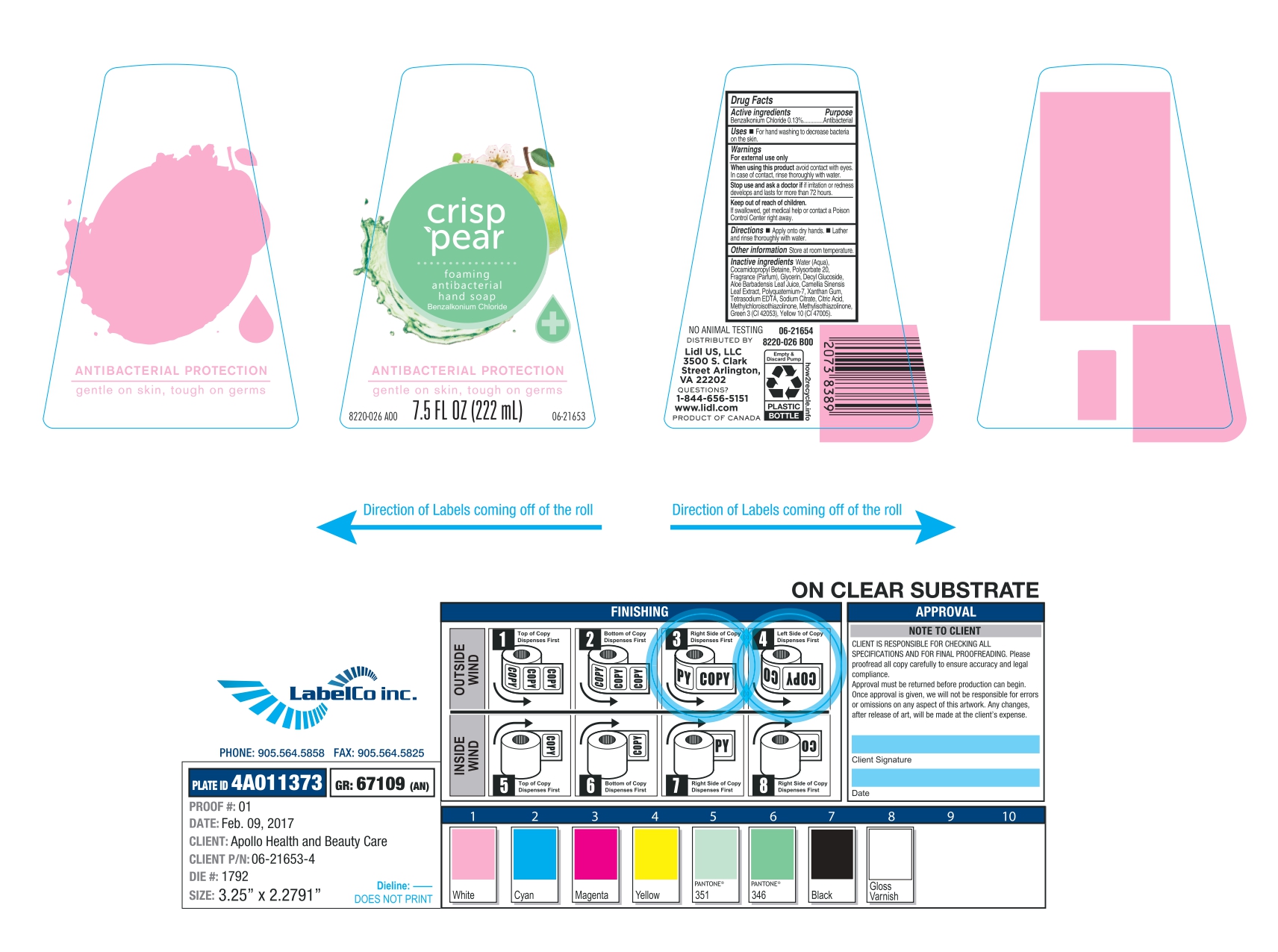 DRUG LABEL: crisp pear
NDC: 71141-022 | Form: SOAP
Manufacturer: LIDL US LLC
Category: otc | Type: HUMAN OTC DRUG LABEL
Date: 20241020

ACTIVE INGREDIENTS: BENZALKONIUM CHLORIDE 130 mg/100 mL
INACTIVE INGREDIENTS: FD&C GREEN NO. 3; MORDANT YELLOW 10; SODIUM CITRATE; COCAMIDOPROPYL BETAINE; POLYSORBATE 20; GLYCERIN; DECYL GLUCOSIDE; ALOE VERA LEAF; CAMELLIA SINENSIS FLOWER; POLYQUATERNIUM-7 (70/30 ACRYLAMIDE/DADMAC; 1600000 MW); XANTHAN GUM; METHYLCHLOROISOTHIAZOLINONE; WATER; METHYLISOTHIAZOLINONE; FRAGRANCE CLEAN ORC0600327; CITRIC ACID MONOHYDRATE; EDETATE SODIUM

NDC- 71141-022-02.

Active Ingredient.

Benzalkonium Chloride (0.13%)

Purpose

Antibacterial

Uses

- For hand washing to decrease bacteria on the skin

Warnings

For external use only

When using this product

Avoid contact with eyes. In case of contact, rinse thoroughly with water.

Stop use and ask a doctor

If irritation or redness develops and lasts for more than 72 hours

Keep out of reach of children.

If swallowed, get medical help or contact a Poison Control Center right away.

Directions

- Apply onto dry hands
- Lather and rinse thoroughly with water.

Other Information

Store at room temperature

Inactive Ingredients

Water (Aqua), Cocamidopropyl Betaine, Polysorbate 20, Fragrance (Parfum), Glycerin, Decyl Glucoside, Aloe Barbadensis Leaf Juice, Camellia Sinensis Leaf Extract, Polyquatermium-7, Xanthan Gum, Tetrasodium EDTA, Sodium Citrate, Citric Acid, Methylchloroisothiazolinone, Methylisothiazolinone, Green 3 (Cl 42053), Yellow 10 (Cl 47005)